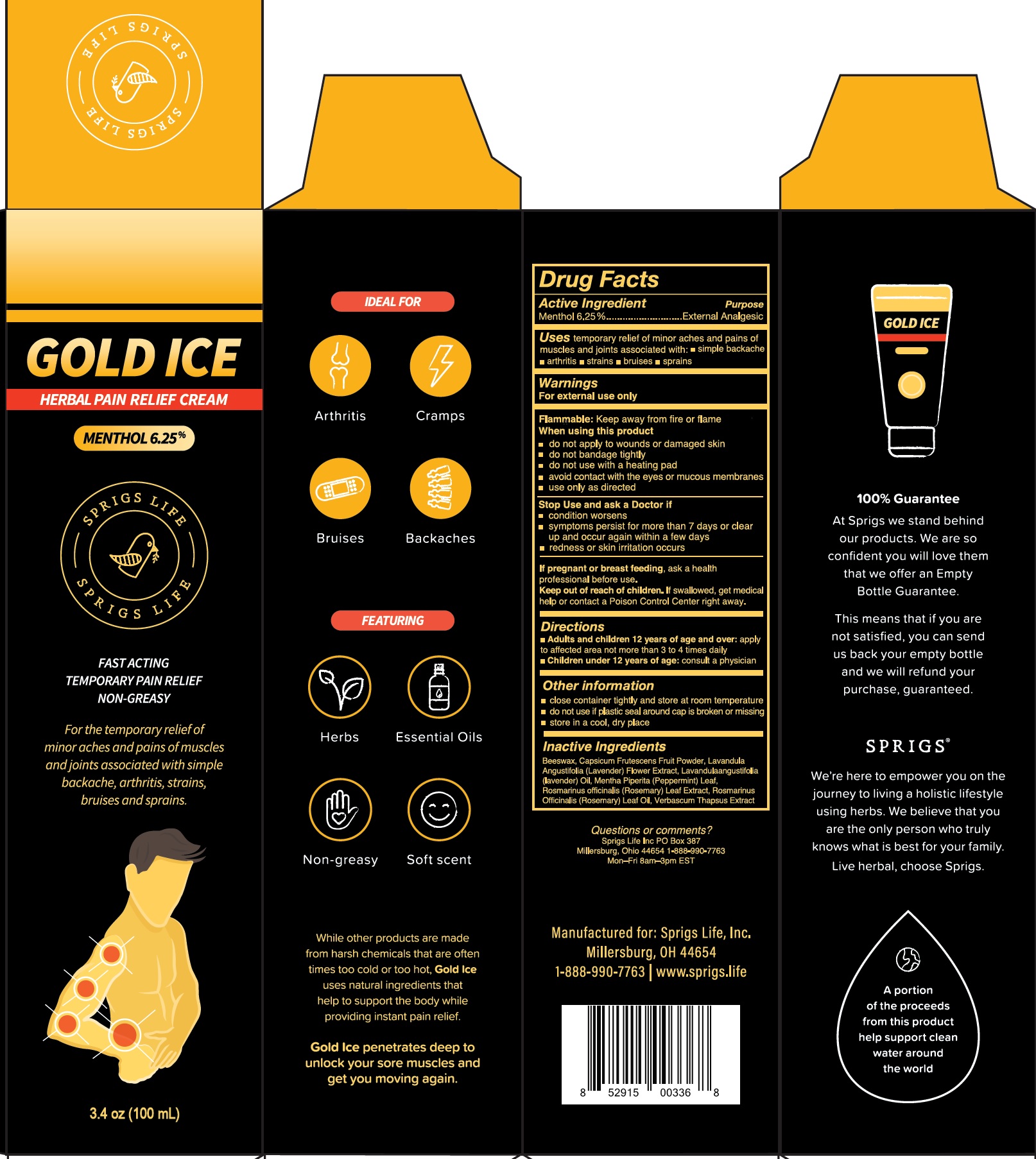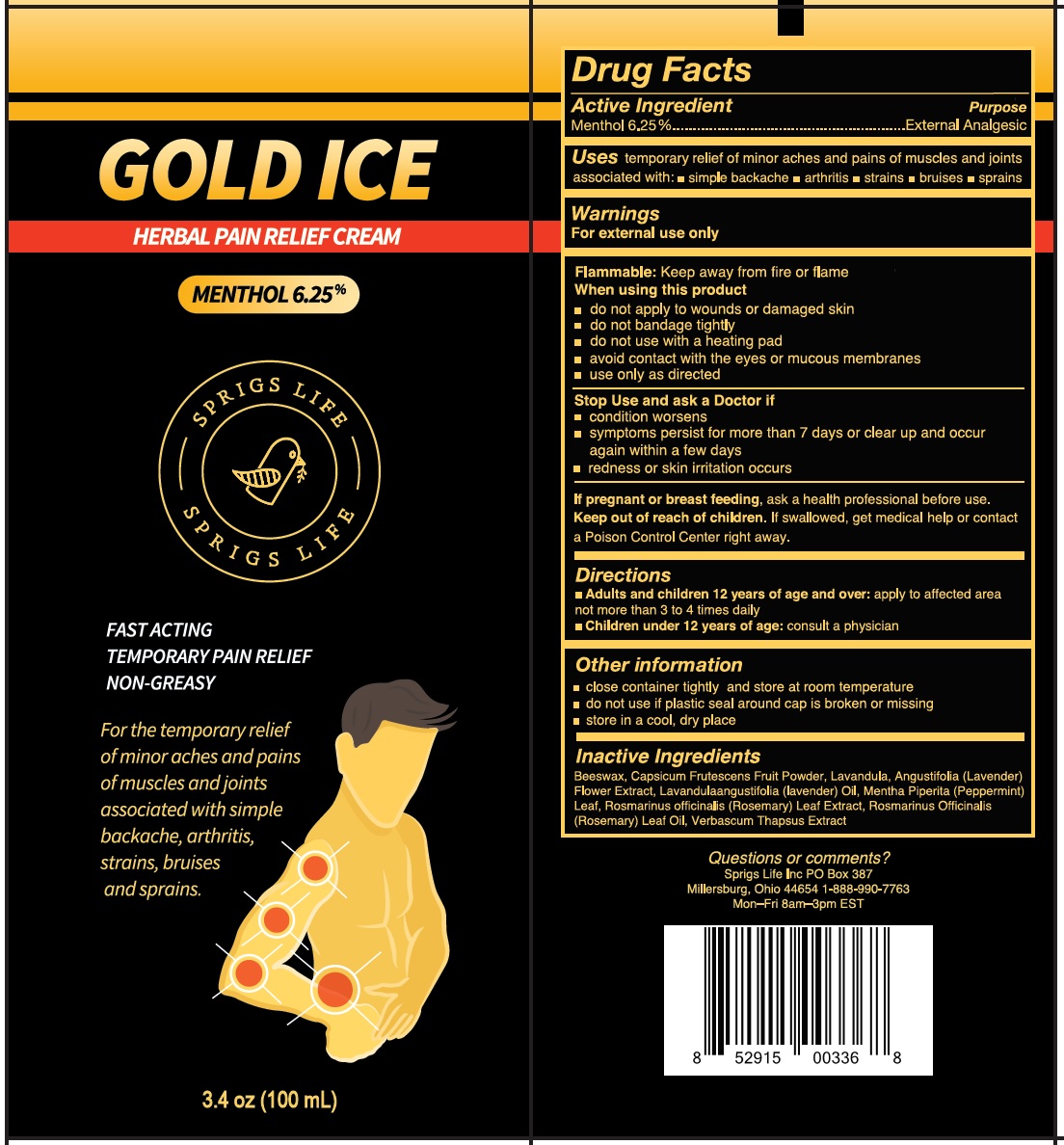 DRUG LABEL: GOLD ICE Pain Relief
NDC: 72226-305 | Form: CREAM
Manufacturer: Eden's Answers, Inc.
Category: otc | Type: HUMAN OTC DRUG LABEL
Date: 20231111

ACTIVE INGREDIENTS: MENTHOL 62.5 mg/1 mL
INACTIVE INGREDIENTS: YELLOW WAX; TABASCO PEPPER; LAVANDULA ANGUSTIFOLIA SUBSP. ANGUSTIFOLIA FLOWER; LAVENDER OIL; MENTHA PIPERITA LEAF; ROSEMARY; ROSEMARY OIL; VERBASCUM THAPSUS WHOLE

GOLD ICE Pain Relief Cream

Active Ingredient

Menthol 6.25%

Purpose

External Analgesic

Uses

temporary relief of minor aches and pains of muscles and joints associated with:

- simple backache
- arthritis
- strains
- bruises
- sprains

Warnings:

For external use only

Keep away from fire or flame Flammable:

When using this product

- do not apply to wounds or damaged skin
- Do not bandage tightly
- do not use with a heating pad
- avoid contact with the eyes or mucous membranes
- use only as directed

Stop Use and ask a Doctor if

- condition worsens
- symptoms persist for more than 7 days or clears up and occur again within a few days.
- redness or skin irritation occurs

If pregnant or breast-feeding,

ask a health professional before use.

Keep out of reach of children.

If swallowed, get medical help or contact a Poison Control Center right away.

Directions

apply to affected area not more than 3 to 4 times daily Adult and children 12 years of age and over:

consult a physician Children under 12 years of age:

Other information

- close container tightly and store at room temperature
- do not use if plastic seal around cap is broken or missing
- store in a cool, dry place

Inactive Ingrediets

Beeswax, Capsicum Frutescens Fruit Powder, Lavandula Angustifolia (Lavender) Flower Extract, Lavandulaangustifolia (lavender) Oil, Mentha Piperita (Peppermint) Leaf, Rosmarinus officinalis (Rosemary) Leaf Extract, Rosmarinus Officinalis (Rosemary) Leaf Oil, Verbascum Thapsus Extract

Questions or Comments?

Sprigs Life Inc PO Box 387

Millersburg, Ohio 44654 1-888-990-7763

Mon-Fri 8am-3pm EST